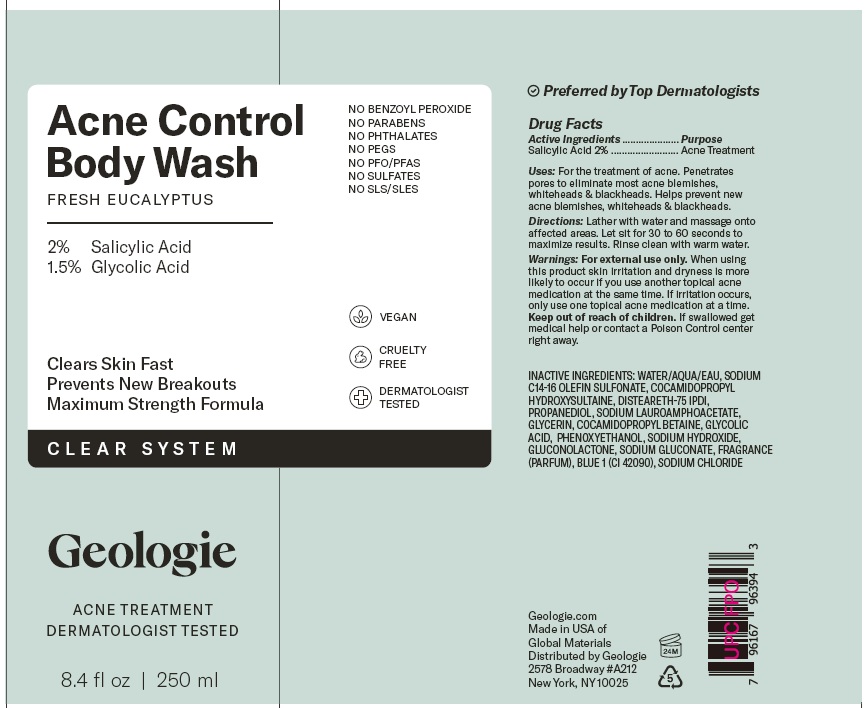 DRUG LABEL: Acne Control Body Wash
NDC: 54111-184 | Form: GEL
Manufacturer: Bentley Laboratories, LLC
Category: otc | Type: HUMAN OTC DRUG LABEL
Date: 20241128

ACTIVE INGREDIENTS: SALICYLIC ACID 2.0 g/100 mL
INACTIVE INGREDIENTS: WATER; SODIUM C14-16 OLEFIN SULFONATE; COCAMIDOPROPYL HYDROXYSULTAINE; DISTEARETH-75 IPDI; PROPANEDIOL; SODIUM LAUROAMPHOACETATE; GLYCERIN; COCAMIDOPROPYL BETAINE; GLYCOLIC ACID; PHENOXYETHANOL; SODIUM HYDROXIDE; GLUCONOLACTONE; SODIUM GLUCONATE; BLUE 1; SODIUM CHLORIDE

Geologie Acne Control Body Wash

DRUG FACTS

Active Ingredients........... Salicylic Acid 2%

Purpose ............... Acne Treatment

INDICATIONS AND USAGE

Uses: For the treatment of acne. Penetrates pores to eliminate most acne blemishes, whiteheads & blackheads. Helps prevent new acne blemishes, whiteheads & blackheads.

DOSAGE AND ADMINISTRATION

Directions: Lather with water and massage onto affected areas. Let sit for 30 to 60 seconds to maximize results. Rinse clean with warm water.

WARNINGS

Warnings: For external use only. When using this product skin irritation and dryness is more likely to occur if you use another topical acne medication at the same time. If irritation occurs, only use one topical acne medication at a time.

KEEP OUT OF REACH OF CHILDREN

Keep out of the reach of children. If swallowed get medical help or contact a Poison Control center right away.

INACTIVE INGREDIENTS: WATER/AQUA/EAU, SODIUM
C14-16 OLEFIN SULFONATE, COCAMIDOPROPYL
HYDROXYSULTAINE, DISTEARETH IPDI,
PROPANEDIOL, SODIUM LAUROAMPHOACETATE,
GLYCERIN, COCAMIDOPROPYL BETAINE, GLYCOLIC
ACID, PHENOXYETHANOL, SODIUM HYDROXIDE,
GLUCONOLACTONE, SODIUM GLUCONATE, FRAGRANCE
PARFUM, BLUE 1 (CI 42090), SODIUM CHLORIDE

Geologie Acne Control Body Wash Labeling

Acne Control
Body Wash
FRESH EUCALYPTUS

2% Salicylic Acid
1.5% Glycolic Acid

8.4 fl oz | 250 ml

Geologie.com
Made in USA of
Global Materials
Distributed by Geologie
2578 Broadway #A212
New York, NY 10025

res